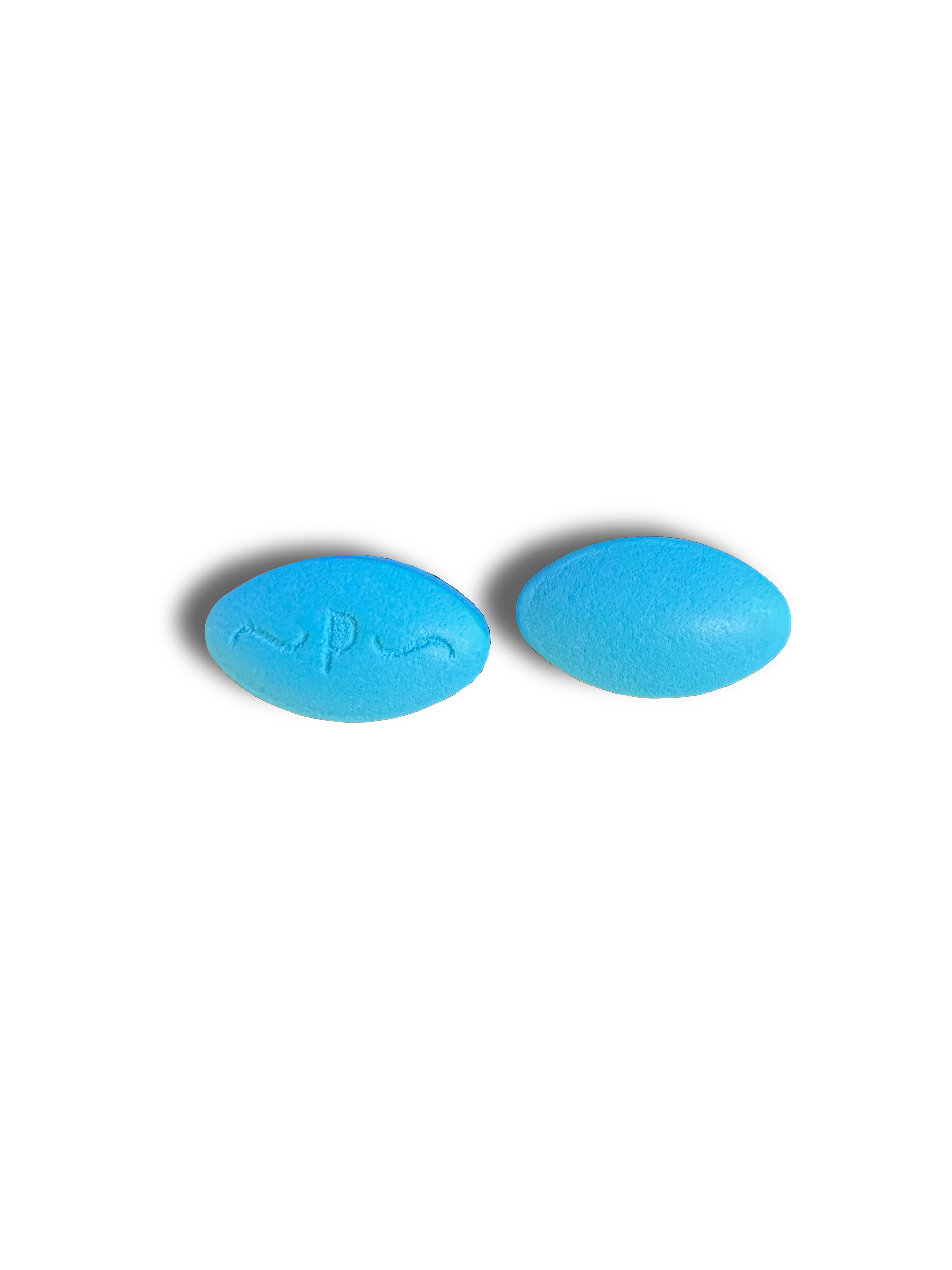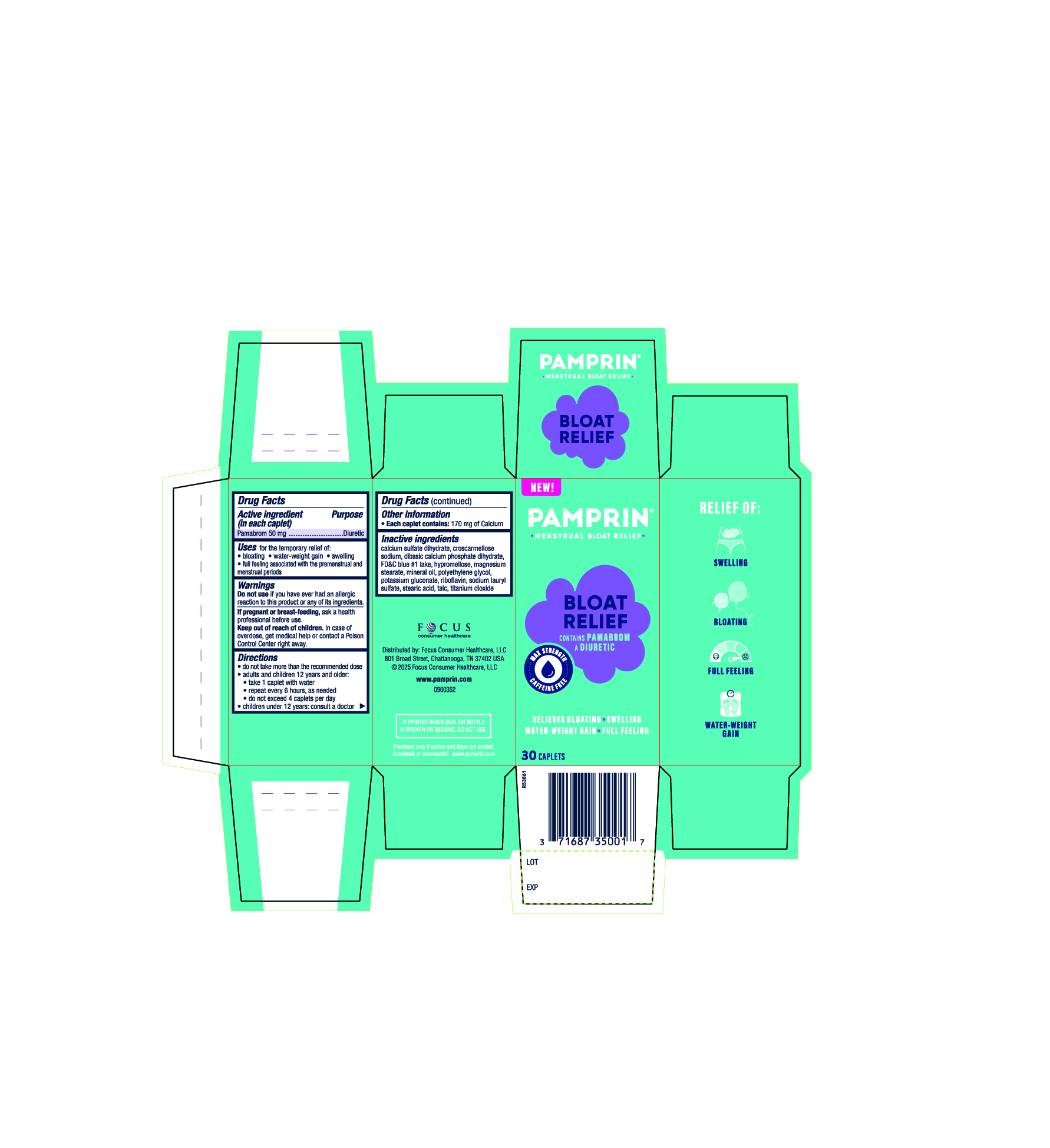 DRUG LABEL: Pamprin
NDC: 71687-3009 | Form: TABLET, FILM COATED
Manufacturer: Focus Consumer Healthcare, LLC
Category: otc | Type: HUMAN OTC DRUG LABEL
Date: 20251231

ACTIVE INGREDIENTS: PAMABROM 50 mg/1 1
INACTIVE INGREDIENTS: CROSCARMELLOSE SODIUM; DIBASIC CALCIUM PHOSPHATE DIHYDRATE; FD&C BLUE NO. 1 ALUMINUM LAKE; HYPROMELLOSES; MAGNESIUM STEARATE; LIGHT MINERAL OIL; POLYETHYLENE GLYCOL 400; POTASSIUM GLUCONATE; CALCIUM SULFATE DIHYDRATE; RIBOFLAVIN; SODIUM LAURYL SULFATE; STEARIC ACID; TITANIUM DIOXIDE; TALC

Pamprin Bloat

Active ingredient (in each caplet)

Pamabrom 50 mg

Purpose

Diuretic

Uses

For the temporary relief of

- bloating
- water-weight gain
- swelling
- full feeling

associated with the premenstrual and menstrual periods.

Do not use if you have ever had an allergic reaction to this product or any of its ingredients.

PREGNANCY OR BREAST FEEDING

If pregnant or breastfeeding, ask a health professional before use.

Keep out of reach of children. In case of overdose, get medical help or contact a Poison Control Center right away.

Directions

- do not take more than the recommended dose
- adults and children 12 years and older:
- take 1 caplet with water
- repeated every 6 hours, as needed
- do not exceed 4 caplets per day
- children under 12 years: consult a doctor

Other information

Each caplet contains: 170 mg of Calcium

Inactive ingredients

calcium sulfate dihydrate, croscarmellose sodium, dibasic calcium phosphate dihydrate, FDC Blue #1 lake, hypromellose, magnesium stearate, mineral oil, polyethylene glycol, potassium gluconate, riboflavin, sodium lauryl sulfate, stearic acid, talc, titanium dioxide